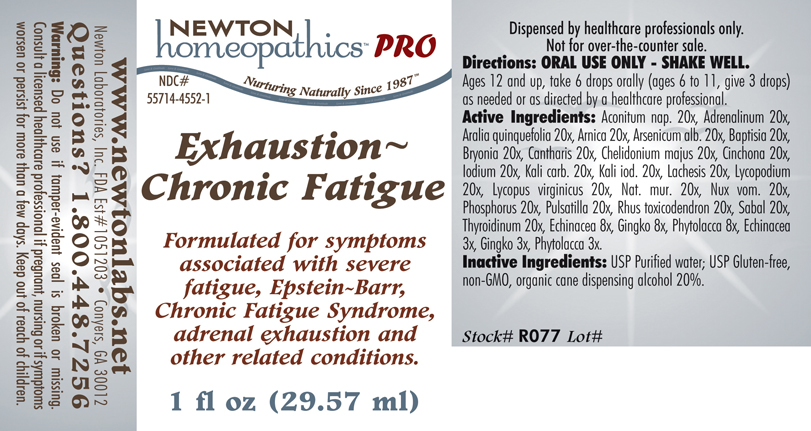 DRUG LABEL: Exhaustion Chronic Fatigue 
NDC: 55714-4552 | Form: LIQUID
Manufacturer: Newton Laboratories, Inc.
Category: homeopathic | Type: HUMAN PRESCRIPTION DRUG LABEL
Date: 20110601

ACTIVE INGREDIENTS: Aconitum Napellus 20 [hp_X]/1 mL; Epinephrine 20 [hp_X]/1 mL; American Ginseng 20 [hp_X]/1 mL; Arnica Montana 20 [hp_X]/1 mL; Arsenic Trioxide 20 [hp_X]/1 mL; Baptisia Tinctoria 20 [hp_X]/1 mL; Bryonia Alba Root 20 [hp_X]/1 mL; Lytta Vesicatoria 20 [hp_X]/1 mL; Chelidonium Majus 20 [hp_X]/1 mL; Cinchona Officinalis Bark 20 [hp_X]/1 mL; Iodine 20 [hp_X]/1 mL; Potassium Carbonate 20 [hp_X]/1 mL; Potassium Iodide 20 [hp_X]/1 mL; Lachesis Muta Venom 20 [hp_X]/1 mL; Lycopodium Clavatum Spore 20 [hp_X]/1 mL; Lycopus Virginicus 20 [hp_X]/1 mL; Sodium Chloride 20 [hp_X]/1 mL; Strychnos Nux-vomica Seed 20 [hp_X]/1 mL; Phosphorus 20 [hp_X]/1 mL; Pulsatilla Vulgaris 20 [hp_X]/1 mL; Toxicodendron Pubescens Leaf 20 [hp_X]/1 mL; Saw Palmetto 20 [hp_X]/1 mL; Thyroid, Unspecified 20 [hp_X]/1 mL; Echinacea, Unspecified 8 [hp_X]/1 mL; Ginkgo 8 [hp_X]/1 mL; Phytolacca Americana Root 8 [hp_X]/1 mL; Echinacea, Unspecified 3 [hp_X]/1 mL; Ginkgo 3 [hp_X]/1 mL; Phytolacca Americana Root 3 [hp_X]/1 mL
INACTIVE INGREDIENTS: Alcohol

Exhaustion Chronic Fatigue

PRODUCT NAME & INDICATIONS SECTION

Exhaustion~Chronic Fatigue Formulated for symptoms associated with severe fatigue, Epstein-Barr, Chronic Fatigue Syndrome, adrenal exhaustion and other related conditions.

DIRECTION SECTION

Directions: ORAL USE ONLY - SHAKE WELL. Ages 12 and up, take 6 drops orally (ages 6 to 11, give 3 drops) as needed or as directed by a healthcare professional.

ACTIVE INGREDIENT SECTION

Aconitum nap. 20x, Adrenalinum 20x, Aralia quinquefolia 20x, Arnica 20x, Arsenicum alb. 20x, Baptisia 20x, Bryonia 20x, Cantharis 20x, Chelidonium majus 20x, Cinchona 20x, Iodium 20x, Kali carb. 20x, Kali iod. 20x, Lachesis 20x, Lycopodium 20x, Lycopus virginicus 20x, Nat. mur. 20x, Nux vom. 20x, Phosphorus 20x, Pulsatilla 20x, Rhus toxicodendron 20x, Sabal 20x, Thyroidinum 20x, Echinacea 8x, Gingko 8x, Phytolacca 8x, Echinacea 3x, Gingko 3x, Phytolacca 3x.

PURPOSE SECTION

Formulated for symptoms associated with severe fatigue, Epstein-Barr, Chronic Fatigue Syndrome, adrenal exhaustion and other related conditions.

INACTIVE INGREDIENT SECTION

Inactive Ingredients: USP Purified Water; USP Gluten-free, non-GMO, organic cane dispensing alcohol 20%.

QUESTIONS? SECTION

www.newtonlabs.net Newton Laboratories, Inc. FDA Est # 1051203 -Conyers, GA 30012
Questions? 1.800.448.7256

WARNINGS SECTION

Warning: Do not use if tamper - evident seal is broken or missing. Consult a licensed healthcare professional if pregnant, nursing or if symptoms worsen or persist for more than a few days. Keep out of reach of children.

OTC - PREGNANCY OR BREAST FEEDING SECTION

Consult a licensed healthcare professional if pregnant, nursing or if symptoms worsen or persist for more than a few days.

OTC - KEEP OUT OF REACH OF CHILDREN SECTION

Keep out of reach of children.